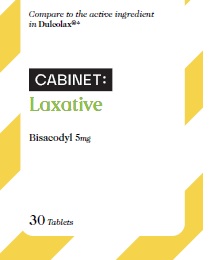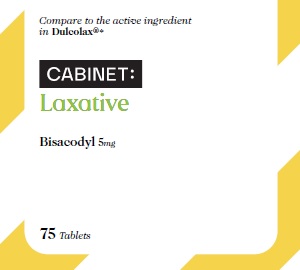 DRUG LABEL: Bisacodyl
NDC: 68210-4106 | Form: TABLET
Manufacturer: Spirit Pharmaceuticals LLC
Category: otc | Type: HUMAN OTC DRUG LABEL
Date: 20241210

ACTIVE INGREDIENTS: BISACODYL 5 mg/1 1
INACTIVE INGREDIENTS: ACACIA; CALCIUM SULFATE ANHYDROUS; ANHYDROUS LACTOSE; CARNAUBA WAX; SILICON DIOXIDE; STARCH, CORN; D&C YELLOW NO. 10; FD&C YELLOW NO. 6; GELATIN; FERRIC OXIDE RED; FERRIC OXIDE YELLOW; FERROSOFERRIC OXIDE; MAGNESIUM STEARATE; MICROCRYSTALLINE CELLULOSE; POLYETHYLENE GLYCOL 400; POLYVINYL ACETATE PHTHALATE; POVIDONE K30; SHELLAC; SODIUM STARCH GLYCOLATE TYPE A CORN; STEARIC ACID; TALC; TITANIUM DIOXIDE; SUCROSE

Bisacodyl Tablets

Active ingredient (in each tablet)

Bisacodyl (USP) 5 mg

Purpose

Stimulant laxative

Uses

- for temporary relief of occasional constipation and irregularity
- this product generally produces bowel movement in 6 to 12 hours

Warnings

Do not use if you cannot swallow without chewing

Ask a doctor before use if you have

■ stomach pain, nausea or vomiting
■ a sudden change in bowel habits that lasts more than 2
weeks

When using this product

■ do not chew or crush tablet(s)
■ it may cause stomach discomfort, faintness and cramps
■ do not use within 1 hour after taking an antacid or milk

Stop use and ask a doctor if

■ you have rectal bleeding or no bowel movement after
using this product. These could be signs of a serious
condition.
■ you need to use a laxative for more than 1 week

PREGNANCY OR BREAST FEEDING

Ifpregnant or breast-feeding, ask a health professional before use.

Keep out of reach of children.

Directions

- take with a glass of water

adults and children 12 years and over | 1 to 3 tablets in a single daily dose
children 6 to under 12 years of age | 1 tablet in a single daily dose
children under 6 years of age | ask a doctor

Other information
■ each tablet contains: magnesium 5 mg
■ store at 20-25°C (68-77°F)
■ protect from excessive humidity

Inactive ingredients

Acacia, anhydrous calcium sulfate, anhydrous lactose,
carnauba wax, colloidal silicon dioxide, corn starch, D&C
Yellow #10 Aluminum Lake, FD&C Yellow #6 Aluminum
Lake, gelatin, iron oxide, iron oxide black, iron oxide yellow
(iron oxide ochre), magnesium stearate, microcrystalline
cellulose, polyethylene glycol (PEG) 400, polyvinyl acetate
phthalate, povidone, shellac, sodium starch glycolate, stearic
acid, sugar, talc, titanium dioxide

Questions or comments? 1-888-333-9792

PRINCIPAL DISPLAY PANEL

CABINET

Bisacodyl Tablets,
USP 5 mg